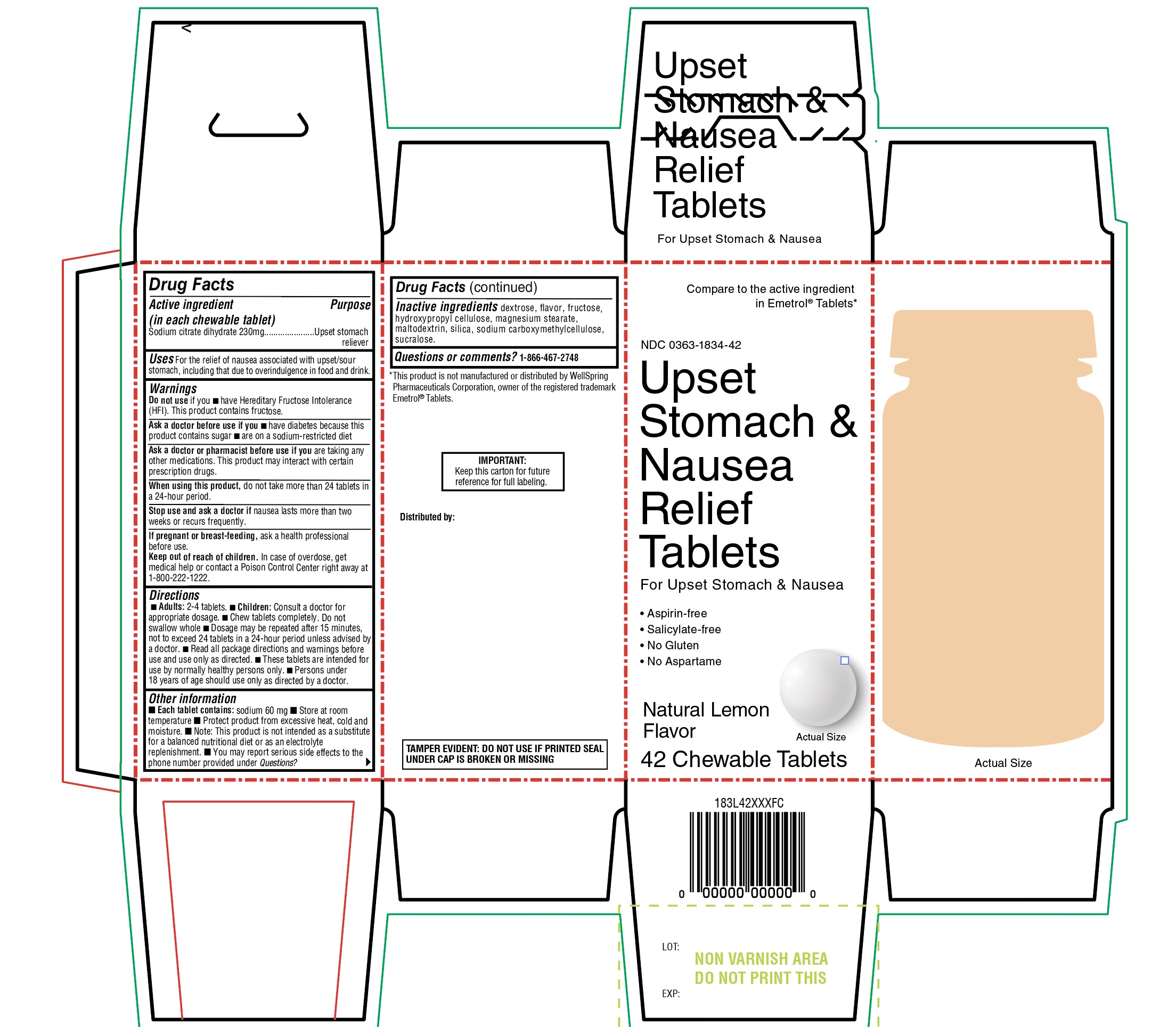 DRUG LABEL: WALGREENS
NDC: 0363-1834 | Form: TABLET, CHEWABLE
Manufacturer: WALGREENS CO.
Category: otc | Type: HUMAN OTC DRUG LABEL
Date: 20260115

ACTIVE INGREDIENTS: TRISODIUM CITRATE DIHYDRATE 230 mg/1 1
INACTIVE INGREDIENTS: DEXTROSE, UNSPECIFIED FORM; LEMON; FRUCTOSE; HYDROXYPROPYL CELLULOSE, UNSPECIFIED; MAGNESIUM STEARATE; MALTODEXTRIN; SILICON DIOXIDE; CARBOXYMETHYLCELLULOSE SODIUM, UNSPECIFIED; SUCRALOSE

Walgreens Upset Stomach & Nausea Relief Tablets

Active ingredients

Sodium citrate dihydrate 230 mg

Purpose

Upset stomach reliever

Uses

For the relief of nausea associated with upset/sour stomach, including that due to overindulgence in food and drink.

Warnings

Do not use if you

- have Hereditary Fructose Intolerance (HFI). This product contains fructose.

Ask a doctor before use if you

- have diabetes because this product contains sugar
- are on a sodium-restricted diet

Ask a doctor or pharmacist before use if you

- are taking any other medications. This product may interact with certain prescription drugs.

When using this product,

- do not take more than 24 tablets in a 24-hour period.

Stop use and ask a doctor if

- nausea lasts more than two weeks or recurs frequently.

If pregnant or breast-feeding,

- ask a health professional before use.

Keep out of reach of children

In case of overdose, get medical help or contact a Poison Control Center right away at 1-800-222-1222.

Directions

- Adults: 2-4 tablets.
- Children: Consult a doctor for appropriate dosage.
- Chew tablets completely. Do not swallow whole
- Dosage may be repeated after 15 minutes, not to exceed 24 tablets in a 24-hour period unless advised by a doctor.
- Read all package directions and warnings before use and use only as directed.
- These tablets are intended for use by normally healthy persons only.
- Persons under 18 years of age should use only as directed by a doctor.

Other information

- Each table contains: Sodium 60mg
- Store at room temperature
- Protect product from excessive heat, cold and moisture
- Note: This product is not intended as a substitute for a balanced nutritional diet or as an electrolyte replenishment.
- You may report serious side effects to the phone number provided under Questions.

Inactive ingredients

dextrose, flavor, fructose, hydroxypropyl cellulose, magnesium stearate, maltodextrin, silica, sodium carboxymethylcellulose, sucralose.

Questions or Comments?

1-866-467-2748

PACKAGE LABEL

Compare to the active ingredient in Emetrol®Tablets*

NDC 0363-1834-42

Upset Stomach & Nausea Relief Tablets

For upset stomach & Nausea

- Aspirin Free
- Salicylate-free
- No Gluten
- No Aspartame

Natural Lemon Flavor

42 Chewable Tablets

IMPORTANT: Keep this carton for future reference for full labeling.

TAMPER EVIDENT: DO NOT USE IF PRINTED SEAL UNDER CAP IS BROKEN OR MISSING.

*This product is not manufactured or distributed by WellSpring Pharmaceuticals Corporation, owner of the registered trademark Emetrol®Tablets.